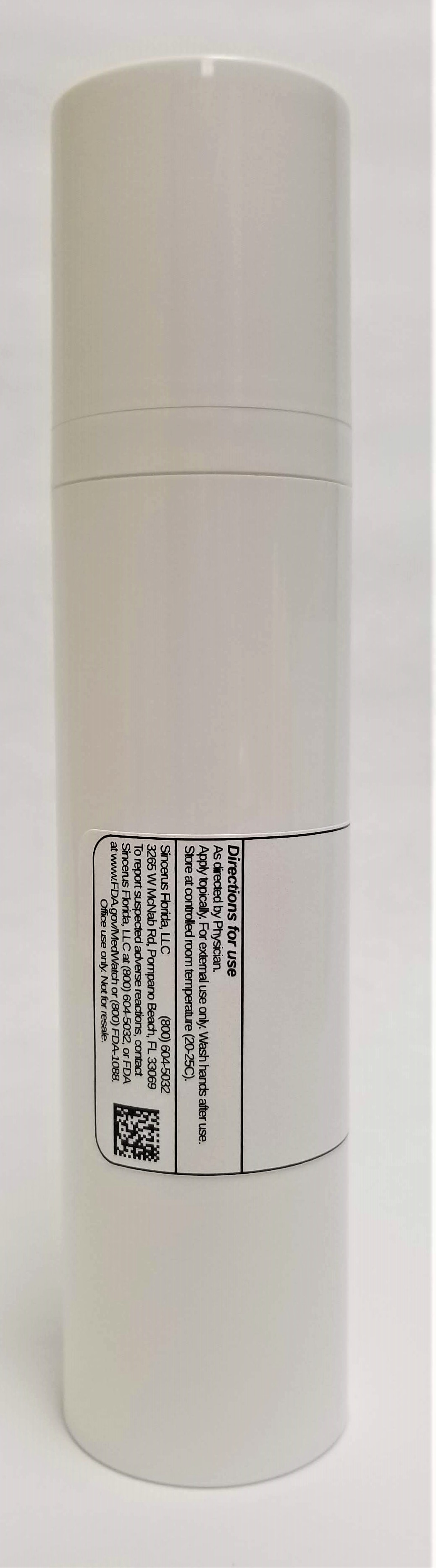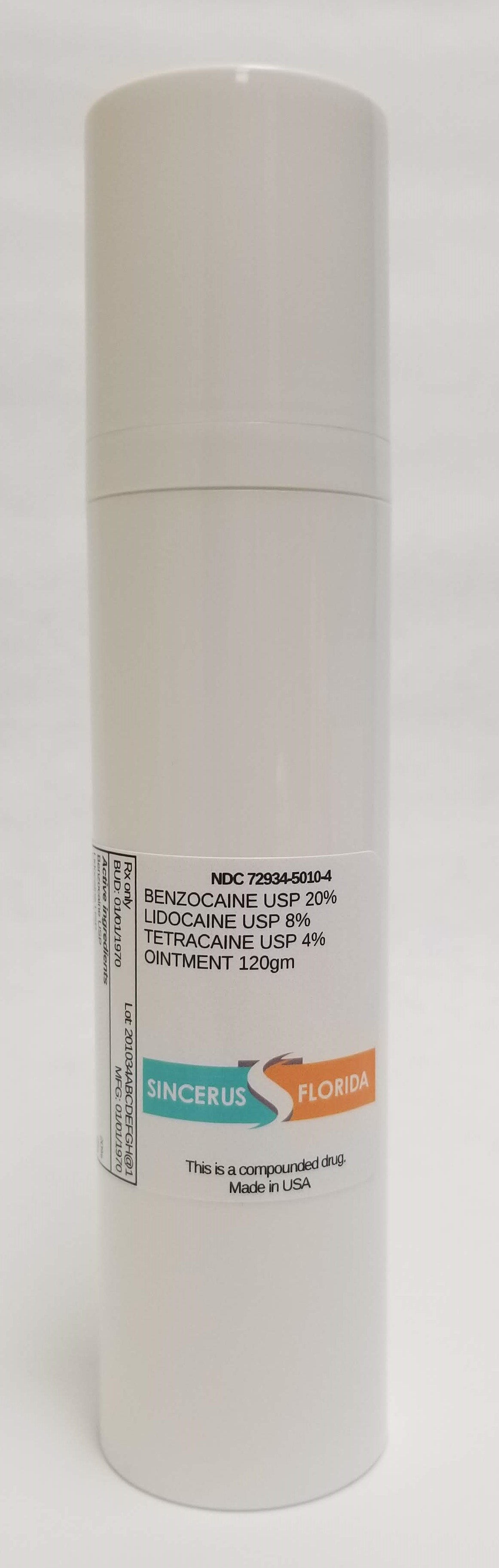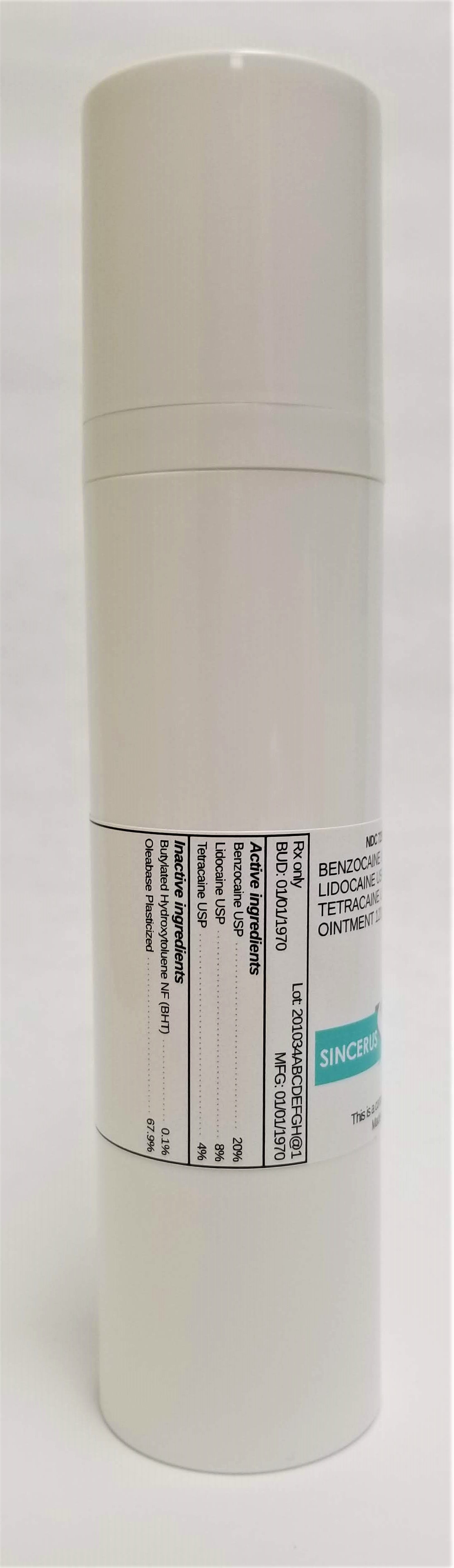 DRUG LABEL: NDC 72934- 5010-4 BENZOCAINE 20% / LIDOCAINE 8% / TETRACAINE 4%.
NDC: 72934-5010 | Form: OINTMENT
Manufacturer: Sincerus Florida, LLC
Category: prescription | Type: HUMAN PRESCRIPTION DRUG LABEL
Date: 20190517

ACTIVE INGREDIENTS: BENZOCAINE 20 g/100 g; LIDOCAINE 8 g/100 g; TETRACAINE 4 g/100 g

BENZOCAINE 20% / LIDOCAINE 8% / TETRACAINE 4%.